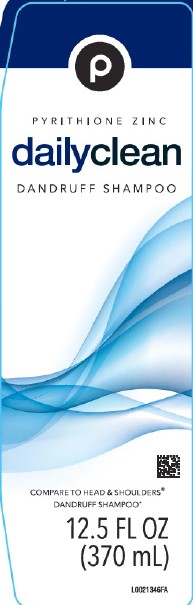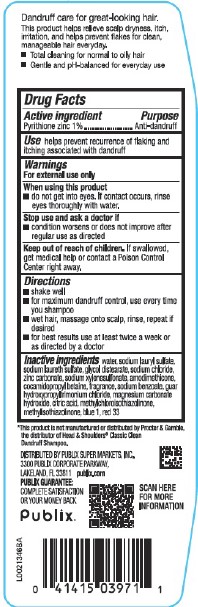 DRUG LABEL: Dandruff
NDC: 56062-153 | Form: SHAMPOO
Manufacturer: Publix Super Markets, Inc.
Category: otc | Type: HUMAN OTC DRUG LABEL
Date: 20260205

ACTIVE INGREDIENTS: PYRITHIONE ZINC 10 mg/1 mL
INACTIVE INGREDIENTS: WATER; SODIUM LAURYL SULFATE; SODIUM LAURETH SULFATE; GLYCOL DISTEARATE; SODIUM CHLORIDE; ZINC CARBONATE; SODIUM XYLENESULFONATE; AMODIMETHICONE (800 CST); COCAMIDOPROPYL BETAINE; SODIUM BENZOATE; GUAR HYDROXYPROPYLTRIMONIUM CHLORIDE (1.7 SUBSTITUENTS PER SACCHARIDE); MAGNESIUM CARBONATE HYDROXIDE; CITRIC ACID MONOHYDRATE; METHYLCHLOROISOTHIAZOLINONE; METHYLISOTHIAZOLINONE; FD&C BLUE NO. 1; D&C RED NO. 33

Publix 153.008/153AZ rev 1, BA, BC, BD
Everyday Clean Dandruff Shampoo

Claims

Dandruff care for great-looking hair.

This product helps relieve scalp dryness, itch, irritation and helps prevent flakes for clean manageable hair everyday.

- Total cleaning for normal to oily hair
- Gentle and pH balanced for everyday use

Active ingredient

Pyrithione zinc 1%

Purpose

Anti-dandruff

Use

helps prevent recurrence of flaking and itching associated with dandruff

Warnings

For external use only

When using theis product

- do not get into eyes. If contact occurs, rinse eyes thoroughly with water.

Stop use and ask a doctor if

- condition worsens or does not improve after regular use as directed

Keep out of reach of children.

If swallowed, get medical help or contact a Poison Control Center right away.

Directions

- shake well
- for maximum dandruff control, use every time you shampoo
- wet hair, massage onto scalp, rinse, repeat if desired
- for best results use at least twice a week or as directed by a doctor

Inactive ingredients

water, sodium lauryl sulfate, sodium laureth sulfate, glycol distearate, sodium chloride, zinc carbonate, sodium xylenesulfonate, amodimethicone, cocamidopropyl betaine, fragrance, sodium benzoate, guar hydroxypropyltrimonium chloride, magnesium carbonate hydroxide, citric acid, methylchloroisothiazolinone, methylisothiazolinone, blue 1, red 33

Dislcaimer

*This product is not manufactured or distributed by Procter & Gamble, distributor of Head & Shoulders® Classic Clean Dandruff Shampoo.

Adverse Reaction

DISTRIBUTED BY PUBLIX SUPER MARKETS, INC

3300 PUBLIX CORPORATE PARKWAY,

LAKELAND, FL 33811

publix.com

PUBLIX GUARANTEE:

COMPLETE SATISFACTION OR YOUR MONEY BACK

Publix

SCAN HERE FOR MORE INFORMATION

Principal display panel

P

PYRITHIONE ZINC

dailyclean

DANDRUFF SHAMPOO

COMPARE TO HEAD & SHOULDERS®DANDRUFF SHAMPOO

12.5 FL OZ (370mL)